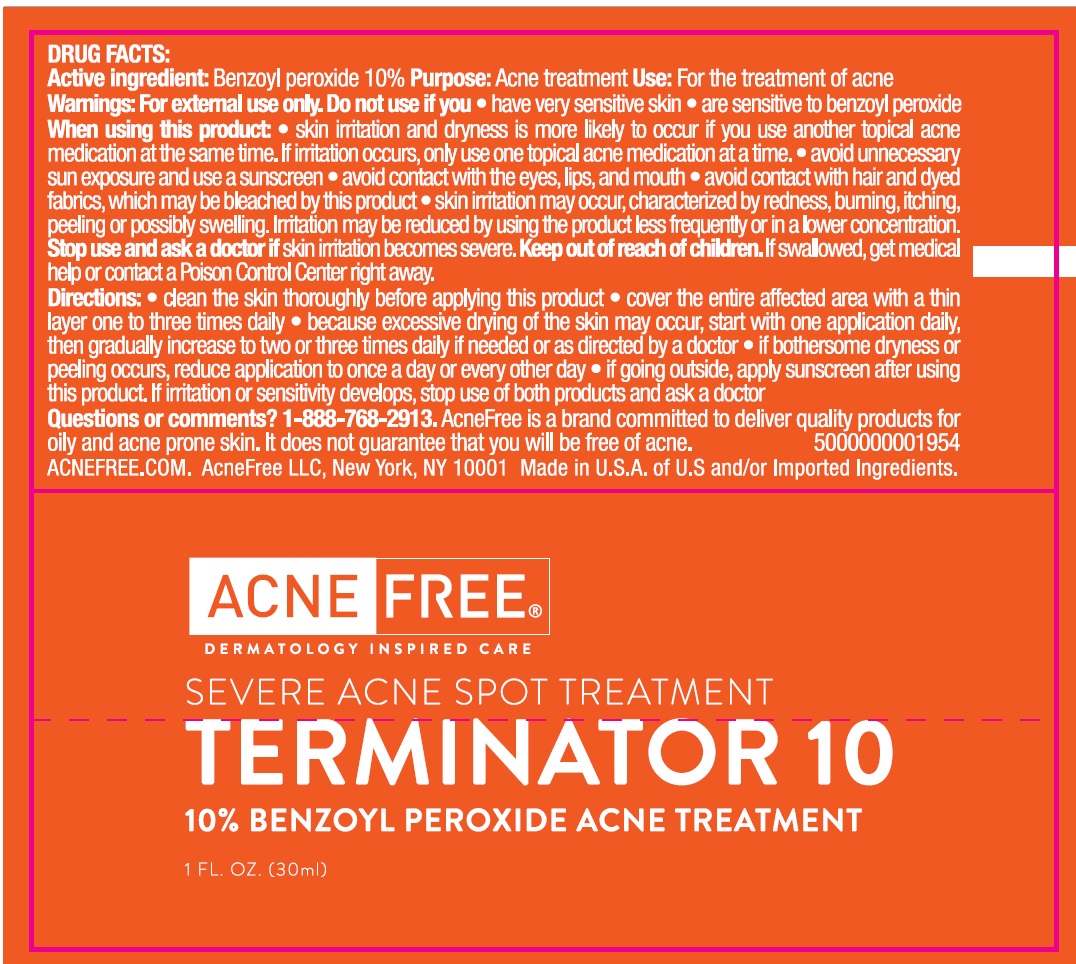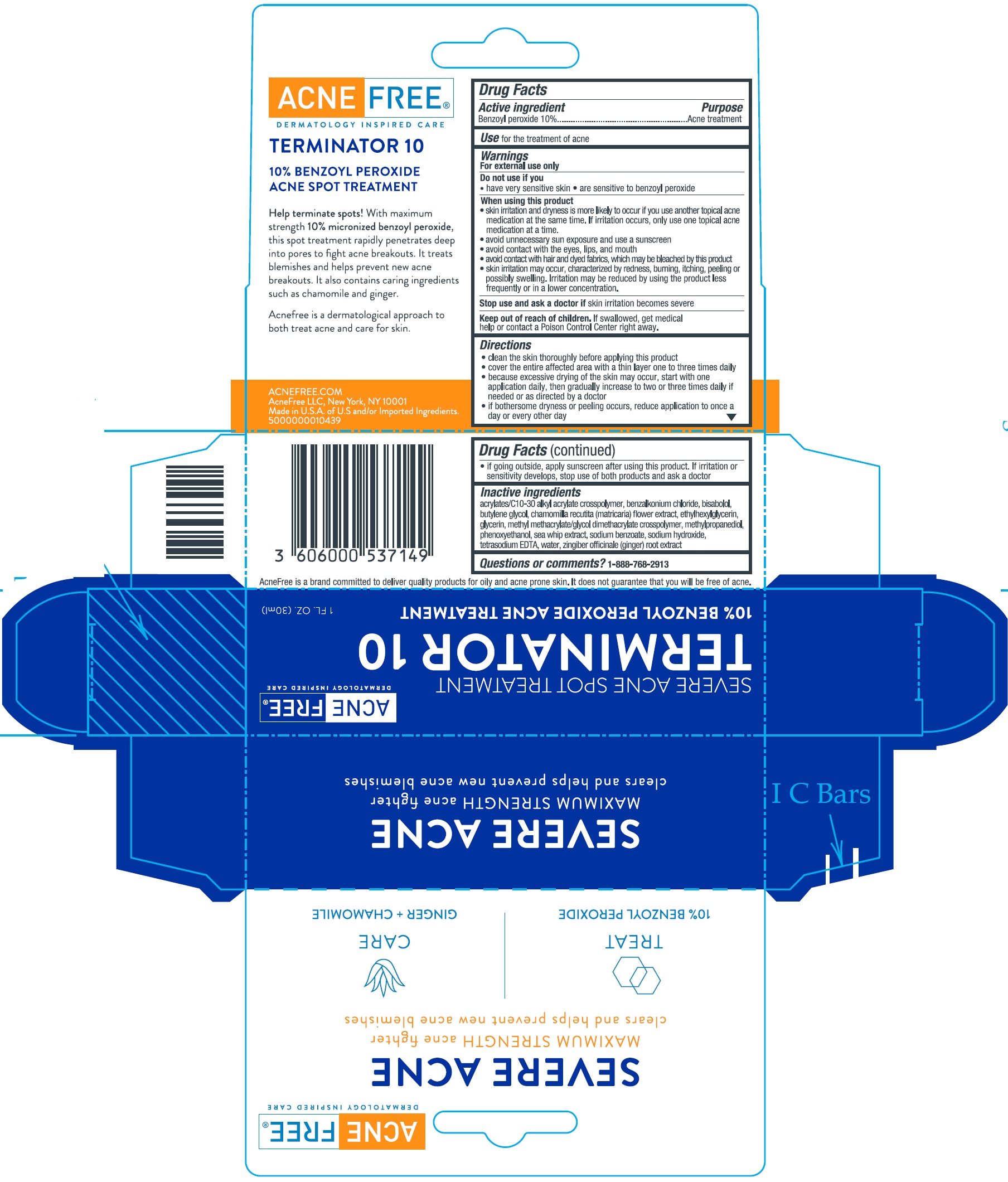 DRUG LABEL: Terminator 10
NDC: 80861-002 | Form: CREAM
Manufacturer: AcneFree, LLC
Category: otc | Type: HUMAN OTC DRUG LABEL
Date: 20250724

ACTIVE INGREDIENTS: BENZOYL PEROXIDE 100 mg/1 mL
INACTIVE INGREDIENTS: CARBOMER INTERPOLYMER TYPE A (ALLYL SUCROSE CROSSLINKED); BENZALKONIUM CHLORIDE; LEVOMENOL; BUTYLENE GLYCOL; CHAMOMILE; ETHYLHEXYLGLYCERIN; GLYCERIN; METHYL METHACRYLATE/GLYCOL DIMETHACRYLATE CROSSPOLYMER; METHYLPROPANEDIOL; PHENOXYETHANOL; PSEUDOPTEROGORGIA ELISABETHAE; SODIUM BENZOATE; SODIUM HYDROXIDE; EDETATE SODIUM; WATER; GINGER

Terminator 10

Active ingredient

Benzoyl peroxide 10%

Purpose

Acne treatment

Use

for the treatment of acne

Warnings

For external use only

Do not use on if you

- have very sensitive skin
- are sensitive to benzoyl peroxide

When using this product

- skin irritation and dryness is more likely to occur if you use another topical acne medication at the same time. If irritation occurs, only use one topical acne medication at a time.
- avoid unnecessary sun exposure and a sunscreen
- avoid contat with the eyes, lips, and mouth
- avoid contact with hair and dyed fabrics, which may be bleached by this product
- skin irritation may occur, characterized by redness, burning, itching, peeling or possibly swelling. Irritation may be reduced by using the product less frequently or in a lower concentration.

Stop use and ask a doctor if

skin irritation becomes severe

Keep out of reach of children.

If swallowed, get medical help or contact a Poison Control Center right away.

Directions

- clean the skin thoroughly before applying this product
- cover the entire affected area with a thin layer one to three times daily
- because excessive drying of the skin may occur, start with one application daily, then gradually increase to two or three times daily if needed or as directed by a doctor
- if bothersome dryness or peeling occurs, reduce application to once a day every other day
- if going outside, apply sunscreen after using this product. If irritation or sensitivity develops, stop use of both products and ask a doctor

Inactive ingredients

acrylates/C10-30 alkyl crosspolymer, benzalkonium chloride, bisabolol, butylene glycol, chamomilla recutita (matricaria) flower extract, ethylhexylglycerin, glycerin, methyl methacrylate/glycol dimethacrylate crosspolymer, methylpropanediol, phenoxyethanol, sea whip extract, sodium benzoate, sodium hydroxide, tetrasodium EDTA, water, zingiber officinale (ginger) root extract

Questions or comments?

1-888-768-2913